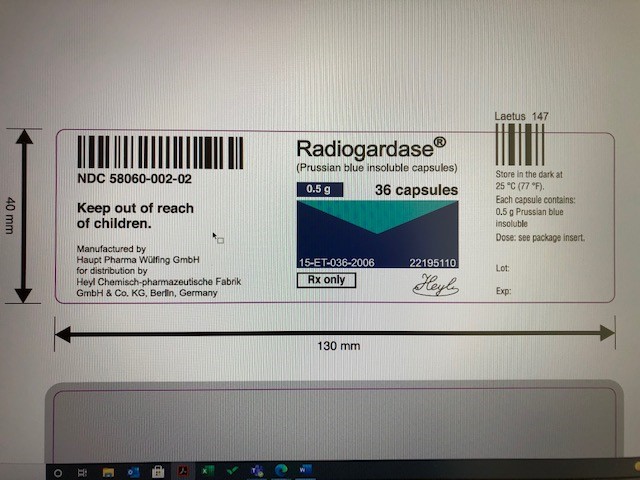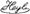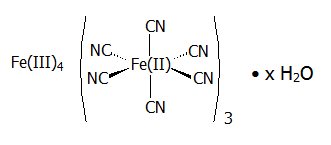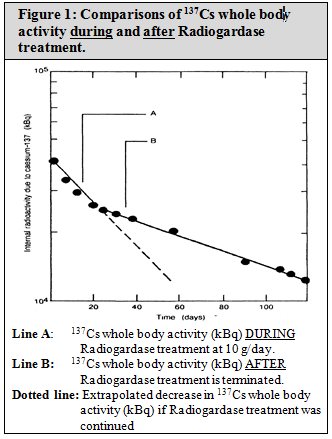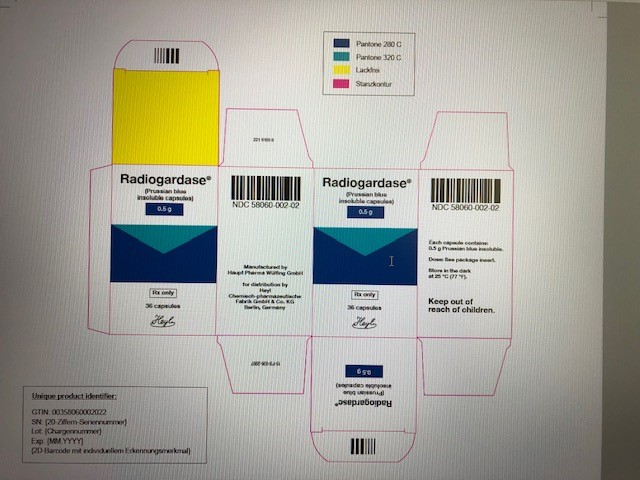 DRUG LABEL: Radiogardase
NDC: 58060-002 | Form: CAPSULE
Manufacturer: Heyl Chem.-pharm. Fabrik GmbH & Co. KG
Category: prescription | Type: HUMAN PRESCRIPTION DRUG LABEL
Date: 20211007

ACTIVE INGREDIENTS: FERRIC FERROCYANIDE 500 mg/1 1
INACTIVE INGREDIENTS: CELLULOSE, MICROCRYSTALLINE 38 mg/1 1; GELATIN 83.12 mg/1 1; WATER 14.21 mg/1 1; INDIGOTINDISULFONATE SODIUM 0.67 mg/1 1; SODIUM LAURYL SULFATE 0.15 mg/1 1

HIGHLIGHTS OF PRESCRIBING INFORMATION

These highlights do not include all the information needed to use RADIOGARDASE safely and effectively. See full prescribing information for RADIOGARDASE.
RADIOGARDASE (prussian blue insoluble) capsules, for oral use
Initial U.S. Approval: 2003

1 INDICATIONS AND USAGE

Radiogardase is indicated for treatment of patients with known or suspected internal contamination with radioactive cesium and/or radioactive or non-radioactive thallium to increase their rates of elimination. (1)

2 DOSAGE AND ADMINISTRATION

- Adults and Adolescents: 3 grams orally three times a day (2.3)
- Pediatrics (2 – 12 years): 1 gram orally three times a day (2.3)
- Administer as soon as possible after internal contamination with cesium or thallium is suspected (2.1)

3 DOSAGE FORMS AND STRENGTHS

Capsules: 0.5 grams (3)

4 CONTRAINDICATIONS

None (4)

5 WARNINGS AND PRECAUTIONS

- Increased radiation absorbed dose to gastrointestinal mucosa: Monitor for decreased gastrointestinal motility (5.1)
- Constipation: Monitor and treat (5.2)
- Electrolyte abnormalities: Monitor serum electrolytes during treatment (5.3)
- Blue discoloration of stool, oral mucosa and dentition (5.4)

6 ADVERSE REACTIONS

Most common adverse reaction (incidence >24%) was constipation (6)

To report SUSPECTED ADVERSE REACTIONS, contact info@heyl-berlin.de, Fax +49 30 817 4049 or FDA at 1-800-FDA-1088 or www.fda.gov/medwatch.

FULL PRESCRIBING INFORMATION

1 INDICATIONS AND USAGE

Radiogardase is indicated for treatment of patients with known or suspected internal contamination with radioactive cesium and/or radioactive or non-radioactive thallium, in order to increase their rates of elimination.

2 DOSAGE AND ADMINISTRATION

2.1 Important Administration Instructions

- Obtain quantitative baseline of the internalized contamination by radioactive cesium (137Cs) and/or thallium by appropriate whole-body counting and/or by bioassay (e.g., biodosimetry), or feces/urine samples, whenever possible prior to Radiogardase treatment.
- Initiate treatment with Radiogardase as soon as possible after contamination is suspected. Even when delayed, treatment with Radiogardase is effective and should not be withheld.
- Take Radiogardase capsules with food to stimulate excretion of cesium or thallium.
- In patients who cannot tolerate swallowing large numbers of capsules, open the capsules and mix with bland food or liquids.

2.2 Decontamination Procedures for Radioactive Cesium or Thallium Contamination

Prior to initiating treatment with Radiogardase, follow radioactive decontamination safety procedures including:

- Use appropriate radiation protective attire and closely monitor personnel and treatment area for radiation levels using radiation detection, indication, and computation devices (RADIAC) or thermal luminescent devices (TLD).
- Control spread of radiation contamination through the establishment of a patient decontamination area and a contaminated material disposal site (with proper labeling, handling, and disposal of contaminated material).

2.3 Recommended Dosage

- Adults and Adolescents: 3 grams (6 capsules) taken orally three times a day (a total daily dose of 9 grams)
- Pediatric Patients (2 – 12 years): 1 gram (2 capsules) taken orally three times a day (a total daily dose of 3 grams)

2.4 Treatment of Radioactive Cesium Contamination

- Anticipate that treatment with Radiogardase may last 30 days or longer.
- Base duration of Radiogardase treatment on weekly measurements of radioactivity in urine and fecal samples to monitor cesium elimination rate.
- Obtain weekly laboratory evaluations (complete blood count, serum chemistry and electrolytes).

2.5 Treatment of Radioactive and Non-radioactive Thallium Contamination

- Anticipate that treatment with Radiogardase may last 30 days or longer.
- For radioactive thallium:
  - Base duration of Radiogardase treatment on weekly measurements of radioactivity inurine and fecal samples to monitor thallium elimination rate.
  - Continue Radiogardase treatment until a 24-hour urine thallium test is normal (less than 5 micrograms per liter) and radiation level is acceptable.
- For non-radioactive thallium: Continue Radiogardase treatment until a 24-hour urine thallium test is normal (less than 5 micrograms per liter).
- Obtain weekly laboratory evaluations (complete blood count, serum chemistry and electrolytes).
- In cases of severe thallium intoxication, additional types of treatment may be necessary, such as:
  - Induced emesis, followed by gastric intubation and lavage
  - Forced diuresis until urinary thallium excretion is less than 1 mg/24 hours
  - Charcoal hemoperfusion may be useful during the first 48 hours after thallium ingestion (biodistribution phase).
  - Hemodialysis has also been reported to be effective in thallium intoxication.

3 DOSAGE FORMS AND STRENGTHS

Capsules: 0.5 grams - dark blue capsule is imprinted with the light blue inscription: PB

4 CONTRAINDICATIONS

None

5 WARNINGS AND PRECAUTIONS

5.1 Increased Radiation Absorbed Dose to Gastrointestinal Mucosa

Radiogardase can decrease gastrointestinal motility, thus slowing the transit time of radioactivity in the gastrointestinal tract. The slowed transit time can increase the radiation absorbed dose to the gastrointestinal mucosa.

5.2 Constipation

Radiogardase can cause constipation. Monitor and treat for signs and symptoms of constipation. Patients with disorders associated with decreased gastrointestinal motility are at higher risk.

5.3 Electrolyte Abnormalities

Radiogardase may bind to electrolytes found in the gastrointestinal tract. Hypokalemia, with serum potassium values of 2.5 – 2.9 (normal 3.5 – 5.0), was reported in 3 (7%) of 42 patients during treatement with Radiogardase. Monitor serum electrolytes during Radiogardase treatment, particularly when treating patients with pre-existing cardiac arrhythmias or electrolyte imbalances.

5.4 Blue Discoloration of Feces, Oral Mucosa, and Dentition

Radiogardase is excreted primarily in feces and turns stools blue. When Radiogardase capsules are opened and the contents eaten with food, the oral mucosa and dentition may also be colored blue.

6 ADVERSE REACTIONS

Constipation was reported in 10 (24%) of 42 patients treated with Radiogardase. Severity of constipation was mild in 7 patients and moderate in 3 patients [see Warnings and Precautions (5.2)].

7 DRUG INTERACTIONS

Based on animal data, co-administration of Radiogardase with other decorporation agents does not affect the efficacy of Radiogardase for treatment of internal contamination with radioactive cesium and/or radioactive or non-radioactive thallium.

8 USE IN SPECIFIC POPULATIONS

8.1 Pregnancy

Pregnancy Category C
It is not known whether Radiogardase can cause fetal harm when administered to a pregnant woman or if it can affect reproduction capacity. Animal reproduction studies have not been conducted with prussian blue insoluble. However, since Radiogardase is not absorbed from the gastrointestinal tract, effects on the fetus are not expected.

Radioactive cesium (^137Cs) crosses the human placenta. One patient, contaminated with 0.005 mCi^137Cs during her 4th month of pregnancy, was not treated with Radiogardase. At birth, the concentration of^137Cs was the same in the mother and the infant.

Thallium crosses the human placenta. Reported fetal effects include failure to thrive and death. The toxicity from untreated radioactive cesium or thallium exposure is greater than the potential reproductive toxicity of Radiogardase.

8.3 Nursing Mothers

Studies to determine if Radiogardase is excreted in human milk have not been conducted. Since Radiogardase is not absorbed from the gastrointestinal tract, its excretion in milk is unlikely. However, cesium and thallium are transmitted from mother to infant in breast milk. Women internally contaminated with cesium or thallium should not breastfeed.

8.4 Pediatric Use

Radioactive Cesium Contamination
The safety and efficacy of Radiogardase in the treatment of^137Cs in pediatric patients ages, 2 to 18 years old, was established from data from Radiogardase-treated pediatric patients exposed to^137Cs in the Goiânia, Brazil, contamination incident and from Radiogardase-treated adults exposed to^137Cs [see Clinical Studies (14.1)].

Overall, 27 pediatric patients received Radiogardase in the range of 3 to 10 grams per day in divided doses (the maximum recommended adolescent dosage is 9 grams per day). Radiogardase treatment reduced the whole body effective half-life of^137Cs by 46% in adolescents and by 43% in children aged 4 to 12 years of age. In 12 patients for whom the rate of radiation elimination data are available, the rate was similar to that in adults treated with 3 grams three times daily and in pediatric patients treated with 1 gram three times daily. By body weight, the dose ranged from

0.32 gram/kg in the 12-year old patient (10 gram Radiogardase daily dose, 31 kg weight) to

0.21 gram/kg in the 4 year old patient (3 gram Radiogardase daily dose, 14 kg weight) [see Clinical Studies (14.1)] .

Pediatric patients aged 2 up to 4 years are expected to have biliary and gastrointestinal function that is comparable to that of a 4-year old.

The safety and efficacy of Radiogardase has not been established in the treatment of^137Cs contamination in pediatric patients 0 to 2 years old. There are differences in the developmental maturity of the biliary system and gastrointestinal tract of neonates and infants (0 – 2 years). The dosage-related adverse reactions of Radiogardase on an immature gastrointestinal tract are not known.

Radioactive and Non-Radioactive Thallium Contamination
The safety and efficacy of Radiogardase for the treatment of radioactive and non-radioactive thallium contamination in pediatric patients has not been established.

8.5 Geriatric Use

The safety and efficacy of Radiogardase in patients aged 65 and over have not been evaluated, to determine whether they respond differently from younger subjects.. In general, elderly patients should be monitored closely, reflecting the greater frequency of decreased cardiac function and of concomitant disease or other drug therapy.

8.6 Hepatic Impairment

Radiogardase is not systemically bioavailable and does not rely on hepatic metabolism for activation or inactivation. However, Radiogardase may be less effective in patients with hepatic impairment, due to decreased excretion of cesium and thallium in the bile.

10 OVERDOSAGE

Based on reported adverse reactions and mechanism of action, possible overdosage symptoms may include constipation, obstruction, or severe decrease in electrolytes. Gastric distress was reported in 3 patients treated with 20 gram/day of Radiogardase (approximately 2.2 times the maximum recommended dosage). In these patients, the dose was reduced to 10 gram/day for continued treatment.

11 DESCRIPTION

Radiogardase (prussian blue insoluble) is a decorporation agent for oral use. Radiogardase capsules contain insoluble ferric hexacyanoferrate(II), with an empirical formula of Fe4[Fe(CN)6]3 and a molecular weight of 859.3 Daltons. It is supplied as 0.5 gram of blue powder in gelatin capsules with 0 – 38 mg of microcrystalline cellulose. The dark blue capsule is imprinted with the light blue inscription: PB. The powder may vary from uniformly fine, dark granules to coarse light and dark-colored granules. The structural formula for prussian blue insoluble is shown below.

The crystal structure of prussian blue insoluble is a cubic lattice with the FeII and FeIII atoms occupying the corners of the cube and the cyanide groups positioned on the sides.

12 CLINICAL PHARMACOLOGY

12.1 Mechanism of Action

Prussian blue insoluble, ferric hexacyanoferrate(II), acts by ion-exchange, adsorption, and mechanical trapping within the crystal structure, and has a high affinity for radioactive and non-radioactive cesium and thallium.

Prussian blue insoluble binds cesium and thallium isotopes in the gastrointestinal tract after these isotopes are ingested or excreted in the bile by the liver, thereby reducing gastrointestinal reabsorption (enterohepatic circulation). The rate of cesium and thallium elimination is proportional to the duration and dose of prussian blue insoluble.

12.2 Pharmacodynamics

Cesium-137 (^137Cs)
^137Cs has a physical half-life of 30 years, with a beta energy peak at 174.0 keV. Following entry into the blood, it is distributed uniformly through all body tissues. Approximately 10% of^137Cs is eliminated rapidly with a biological half-life of 2 days; 90% is eliminated more slowly, with a biological half-life of 110 days; and less than 1% of the^137Cs is retained with a biological half-life of about 500 days.^137Cs follows the movement of potassium and is excreted into the intestine, reabsorbed from the gastrointestinal (GI) tract into the blood, then to the bile, where it is excreted again into the GI tract by bile via enterohepatic circulation. Without Radiogardase treatment, about 80% of^137Cs is excreted through the kidneys and about 20% in the feces.

Thallium-201 (^201Tl)
Radioactive thallium (^201Tl) has a physical half-life of 3 days with electron and photon emissions with a gamma energy peak at 167.4 keV. Non-radioactive thallium has a biological half-life of

8 – 10 days.The physiologic transport of thallium follows the same route as potasium and is excreted by bile in enterohepatic circulation. Without Radiogardase treatment, the fecal to urine excretion ratio of thallium is approximately 2:1.

The results of fecal analysis from patients contaminated with^137Cs and treated with Radiogardase showed higher activities of^137Cs in feces, and the associated whole body radioactivity counts showed a more rapid rate of elimination from the body. The effectiveness of Radiogardase for one patient is shown in Figure 1. The whole body content of radioactive material of^137Cs in kilo-Bequerels (kBq) is shown on the y-axis. Time in days is on the x-axis. Line “A” represents the whole body activity of^137Cs during prussian blue insoluble treatment at 10 g/day. The dotted line represents extrapolation of the whole body activity if treatment was continued. Line “B” represents the whole body activity of^137Cs, after prussian blue insoluble was stopped.

12.3 Pharmacokinetics

Absorption/Elimination:
Prussian blue insoluble is not absorbed through the intact gastrointestinal wall. Its clearance from the body depends on the gastrointestinal tract transit time.

Food Effects:
Food effect studies have not been conducted. In animal studies, Prussian blue insoluble was not significantly absorbed. Food may increase the effectiveness of prussian blue insoluble by stimulating bile secretion.

13 NONCLINICAL TOXICOLOGY

13.1 Carcinogenesis, Mutagenesis, Impairment of Fertility

Animal studies have not been performed to evaluate the carcinogenic or mutagenic potential of prussian blue insoluble. No study on impairment of male or female fertility and reproductive performance has been conducted in animals.

13.2 Animal Toxicology and/or Pharmacology

Absorption/Elimination
In an animal study (pigs, n =38), after a single dose of 40 mg of labeled prussian blue insoluble, 99% of the administered prussian blue dose was excreted unchanged in feces. Absorption from multiple doses has not been studied.

In a study using rats (n = 40, mean body weight range of 188 – 219 grams) injected with^137Cs, a dose response relationship was demonstrated for the amount of radiation elimination with prussian blue insoluble at doses of 1 to 50 mg/day (Table 1). There is little difference in radiation elimination rate between prussian blue insoluble at doses of 50 to 100 mg/day. In Table 1, the % of Injected Radiation Dose Remaining is defined as the percentage of the total injected dose of^137Cs remaining in the body at 96 hours post administration.

Table 1: Dose Response Relationship in Rats at 96 Hours
Prussian blue insoluble dose (mg/day) | % Injected^137Cs dose remaining (Range)
Untreated | 58.1 (63.3 – 53.4)
1 | 9.42 (13.2 – 6.72)
10 | 1.17 (1.64 – 0.84)
50 | 0.57 (0.80 – 0.41)
100 | 0.52 (0.73 – 0.37)

In studies of rats, pigs, and dogs that were internally contaminated with cesium and thallium, the presence of the insoluble complexes in the gastrointestinal lumen changed the primary elimination route from the kidney to the feces and increased the rate of elimination of these two contaminants.

14 CLINICAL STUDIES

14.1 Cesium-137 Contamination

In literature reports, 72 people received Radiogardase after exposure to radioactive cesium (^137Cs):

- 46 patients with 137Cs contamination
- 19 patients 137Cs contamination in other incidents
- 7 healthy human subjects who voluntarily ingested trace doses of 137Cs

In a 1987 incident in Goiânia, Brazil, 46 patients with heavy internal contamination with 137Cs were treated with Radiogardase (Table 2). Data on the whole body effective half-life of 137Cs, during and after Radiogardase treatment, was completed on 33 of these 46 patients (see Table 2). Radiogardase reduced the mean whole-body effective half-life of 137Cs by 69%, 46%, and 43% in adults, adolescents, and younger children, respectively.

Table 2 shows the decrease in whole body effective half-life of 137Cs in patients during Radiogardase treatment compared to the half-life of 137Cs after Radiogardase discontinuation (after treatment).

Table 2: Cesium-137 Effective Half-life During and After Treatment with Radiogardase
Group | Age; (years) | Radiogardase Dosage | ^137Cs Effective Half Life
Group | Age; (years) | Radiogardase Dosage | During Radiogardase Treatment | After Radiogardase Treatment
Adults (n=5) | > 18 | 10 grams/day | 26 ± 6 days | 80 ± 15 days; (all 21 adult patients)
Adults (n=10) | > 18 | 6 grams/day | 25 ± 15 days | 80 ± 15 days; (all 21 adult patients)
Adults (n=6) | > 18 | 3 grams/day | 25 ± 9 days | 80 ± 15 days; (all 21 adult patients)
Adolescents (n=5) | 12 -14 | < 10 grams/day | 30 ± 12 days | 62 ± 14 days
Children (n=7) | 4 – 9 | < 3 grams/day | 24 ± 3 days | 42 ± 4 days

Data from additional literature articles including 19 patients contaminated with^137Cs in other incidents and a study of 7 human subjects who voluntarily ingested trace doses of^137Cs showed a similar reduction in whole body effective half-life with Radiogardase treatment.

14.2 Thallium Contamination

Thirty-four patients treated with Radiogardase for non-radioactive thallium poisoning have been reported in the literature. Radiogardase treatment reduced the mean serum biologic half-life of thallium from 8 days to 3 days.

16 HOW SUPPLIED/STORAGE AND HANDLING

Radiogardase is supplied as gelatin capsules containing 0.5 grams of prussian blue insoluble for oral administration. The dark blue capsule is imprinted with the light blue inscription: PB. It is packaged in white plastic containers with a child-resistant tamper-evident closure. Each container contains 36 capsules.

- NDC: 58060-002-02

Storage

Store at 20 °C to 25 °C (68 °F to 77 °F), excursions permitted between 15 °C and 30°C (between 59 °F and 86 °F). Brief exposure to temperatures up to 40 °C (104 °F) may be tolerated, provided the mean kinetic temperature does not exceed 25 °C (77 °F); however, minimize such exposure. [see USP Controlled Room Temperature]

17 PATIENT COUNSELING INFORMATION

Decreased Gastrointestinal Motility
Inform patients that Radiogardase can decrease gastrointestinal motility. This can slow the transit time of cesium or thallium bound to Radiogardase and increase the radiation absorbed dose to the gastrointestinal mucosa. Alert patients to monitor for signs and symptoms of constipation and advise patients to seek medical management if symptoms develop.

Precautions to Mitigate Radiation Exposure
Inform patients of safety measures to be taken to minimize radiation exposure to others or re-exposure to self. This includes instruction on appropriate use of the toilet, hand washing, and handling of items such as clothing that might get contaminated with body fluids.

Discoloration of Stool, Oral Mucosa and Dentition
Inform patients taking Radiogardase that their stools might be blue-colored. Also inform patients that if the Radiogardase capsules are opened and the contents are mixed with food and eaten, the mouth and teeth may be colored blue.

Manufactured by:
Haupt Pharma Wülfing GmbH

Distribution by:
HEYL Chemisch-pharmazeutische
Fabrik GmbH & Co. KG,
Berlin